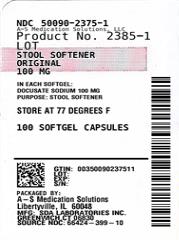 DRUG LABEL: STOOL SOFTNER
NDC: 50090-2375 | Form: CAPSULE, LIQUID FILLED
Manufacturer: A-S Medication Solutions
Category: otc | Type: HUMAN OTC DRUG LABEL
Date: 20210223

ACTIVE INGREDIENTS: DOCUSATE SODIUM 100 mg/1 1
INACTIVE INGREDIENTS: D&C RED NO. 33; FD&C RED NO. 40; FD&C YELLOW NO. 6; GELATIN, UNSPECIFIED; GLYCERIN; POLYETHYLENE GLYCOL, UNSPECIFIED; SORBITOL; TITANIUM DIOXIDE

Drug Facts

Active ingredient (in each softgel)

Docusate sodium 100 mg

Purpose

Stool softener

Uses

- relieves occasional constipation (irregularity)
- generally produces bowel movement in 12 to 72 hours

Warnings

Do not use

if you are presently taking mineral oil, unless told to do so by a doctor

Ask a doctor before use if you have

- stomach pain
- nausea
- vomiting
- noticed a sudden change in bowel habits that lasts over 2 weeks

Stop use and ask a doctor if

- you have rectal bleeding or fail to have a bowel movement after use of a laxative. These could be signs of a serious condition.
- you need to use a stool softener laxative for more than 1 week

If pregnant or breast-feeding,

ask a health professional before use.

Keep out of reach of children.

In case of overdose, get medical help or contact a Poison Control Center right away (1-800-222-1222).

Directions

- take only by mouth. Doses may be taken as a single daily dose or in divided doses.

adults and children 12 years and over | take 1-3 softgels daily
children 2 to under 12 years of age | take 1 softgel daily
children under 2 years | ask a doctor

Other information

- Tamper Evident: do not use if safety seal under cap is broken or missing
- each capsule contains: sodium 6 mg
- VERY LOW SODIUM
- store at 25°C (77°F); excursions permitted between 15o-30oC (59o-86oF).

Keep tightly closed.

This Package for Households Without Young Children

Inactive ingredients

D&C Red #33,Edible ink, FD&C Red #40, FD&C Yellow #6, gelatin, glycerin, polyethylene glycol, purified water, sorbitol special, titanium dioxide

Questions?

Adverse drug event call: (800) 687-0176 Mon- Fri 8 AM to 4 PM

* This product is not manufactured or distributed by Purdue Products L.P., owner of the registered trademark Colace®.

HOW SUPPLIED

Product: 50090-2375

NDC: 50090-2375-1 100 CAPSULE, LIQUID FILLED in a BOTTLE

NDC: 50090-2375-2 60 CAPSULE, LIQUID FILLED in a BOTTLE

NDC: 50090-2375-4 30 CAPSULE, LIQUID FILLED in a BOTTLE